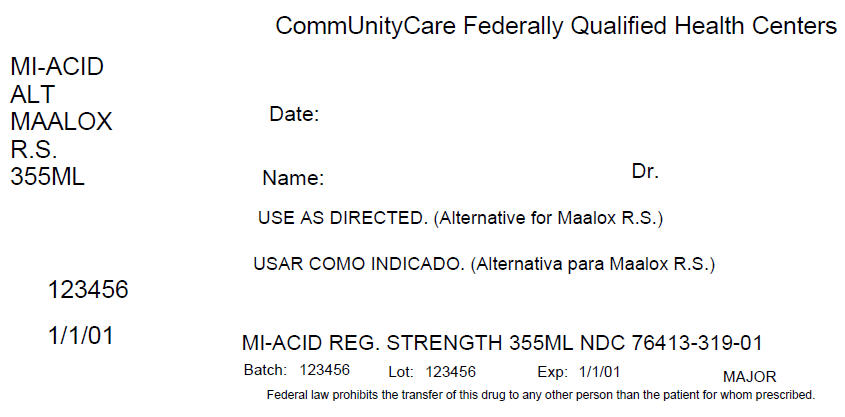 DRUG LABEL: Mi-Acid Regular Strength
NDC: 76413-319 | Form: SUSPENSION
Manufacturer: Central Texas Community Health Centers
Category: otc | Type: HUMAN OTC DRUG LABEL
Date: 20160419

ACTIVE INGREDIENTS: ALUMINUM HYDROXIDE 200 mg/5 mL; MAGNESIUM HYDROXIDE 200 mg/5 mL; DIMETHICONE 20 mg/5 mL
INACTIVE INGREDIENTS: BENZYL ALCOHOL; BUTYLPARABEN; CARBOXYMETHYLCELLULOSE SODIUM, UNSPECIFIED FORM; HYPROMELLOSES; CELLULOSE, MICROCRYSTALLINE; PROPYLPARABEN; WATER; SACCHARIN SODIUM; SORBITOL

Mi-Acid Regular Strength

Active ingredients (in each 5 mL teaspoonful)

Aluminum hydroxide 200 mg (equivalent to dried gel, USP)

Magnesium hydroxide 200 mg

Simethicone 20mg

Purposes

Antacid

Antigas

Uses

relieves

- heartburn
- sour stomach
- acid indigestion
- the symptoms referred to as gas

Warnings

Ask a doctor before use if you have

• kidney disease

• a magnesium-restricted diet

Ask a doctor or pharmacist before use if you are taking a prescription drug.

Antacids may interact with certain prescription drugs.

Stop use and ask a doctor if symptoms last more than 2 weeks

If pregnant or breast-feeding, ask a health professional before use.

Keep out of reach of children.

Directions

• shake well before use

• adults and children 12 years and older: take 2 to 4 teaspoonfuls between meals, at bedtime, or as directed by a doctor

• do not take more than 24 teaspoonfuls in 24 hours or use the maximum dosage for more than 2 weeks

• children under 12 years: ask a doctor

Other information

• each 5 mL teaspoonful contains: magnesium 85 mg, sodium 1 mg

• store at room temperature

• protect from freezing

• keep tightly closed

• TAMPER-EVIDENT: Do not use if breakaway band on bottle is missing or broken.

Inactive ingredients

benzyl alcohol, butylparaben, carboxymethylcellulose sodium, flavor (contains alcohol), hypromellose, microcrystalline cellulose, propylparaben, purified water, saccharin sodium, sorbitol solution

PRINCIPAL DISPLAY PANEL - 355 ML Bottle Label

CommUnityCare Federally Qualified Health Centers

MI-ACID
ALT
MAALOX
R.S.
355ML

Date:

Name:
Dr.

USE AS DIRECTED. (Alternative for Maalox R.S.)

123456

1/1/01

MI-ACID REG. STRENGTH 355ML NDC 76413-319-01

Batch: 123456
Lot: 123456
Exp: 1/1/01
MAJOR

Federal law prohibits the transfer of this drug to any other person than the patient for whom prescribed.